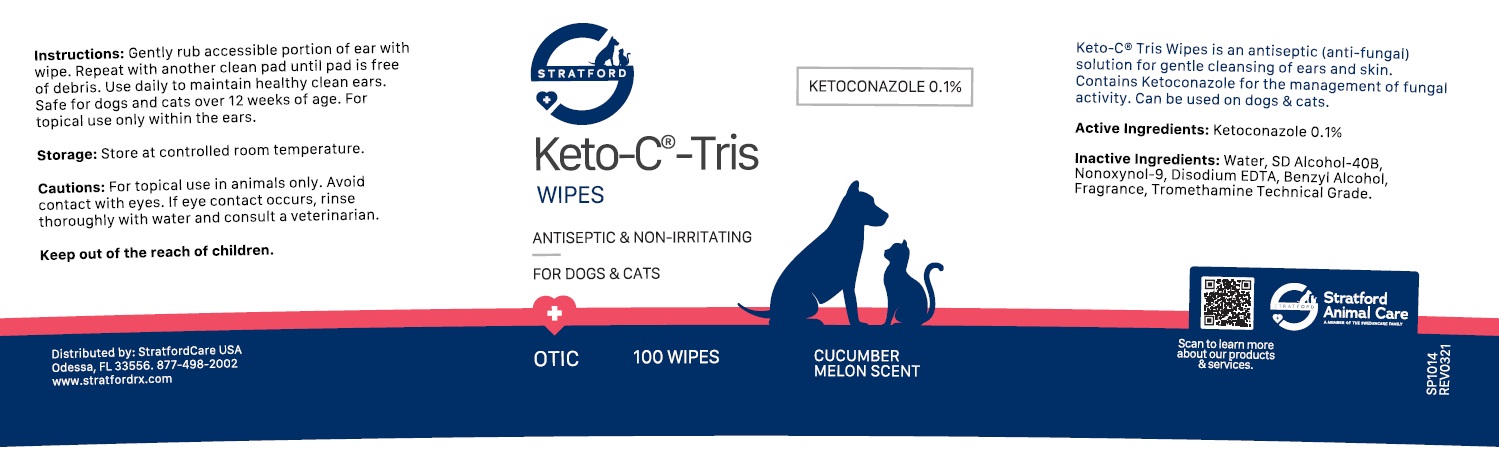 DRUG LABEL: Keto-C-Tris WIPES
NDC: 86069-116 | Form: CLOTH
Manufacturer: Stratford Care Usa, Inc.
Category: animal | Type: OTC ANIMAL DRUG LABEL
Date: 20221121

ACTIVE INGREDIENTS: KETOCONAZOLE 0.1 g/100 g
INACTIVE INGREDIENTS: WATER; ALCOHOL; NONOXYNOL-9; EDETATE DISODIUM ANHYDROUS; BENZYL ALCOHOL; TROMETHAMINE

Keto-C®-Tris WIPES

Active Ingredients: Ketoconazole 0.1%.

PURPOSE

anti-fungal

INDICATIONS AND USAGE

Keto-C® Tris Wipes is an antiseptic (anti-fungal) solution for gentle cleansing of ears and skin. Contains Ketoconazole for the management of fungal activity. Can be used on dogs and cats.

INACTIVE INGREDIENT

Inactive Ingredients: Water, SD Alcohol-40B, Nonoxynol-9, Disodium EDTA, Benzyl Alcohol, Fragrance, Tromethamine Technical Grade.

DOSAGE AND ADMINISTRATION

Instructions: Gently rub accessible portion of ear with wipe. Repeat with another clean pad until pad is free of debris. Use daily to maintain healthy clean ears. Safe for dogs and cats over 12 weeks of age. For topical use only within the ears.

Storage: Store at controlled room temperature.

PRECAUTIONS

Cautions: For topical use in animals only. Avoid contact with eyes. If eye contact occurs, rinse thoroughly with water and consult a veterinarian.

Keep out of the reach of children.

ANTISEPTIC & NON-IRRITATING

FOR DOGS & CATS

CUCUMBER MELON SCENT

Stratford Animal Care
A MEMBER OF THE SWEDENCARE FAMILY

Distributed by: StratfordCare USA
Odessa, FL 33556. 877-498-2002
www.stratfordrx.com